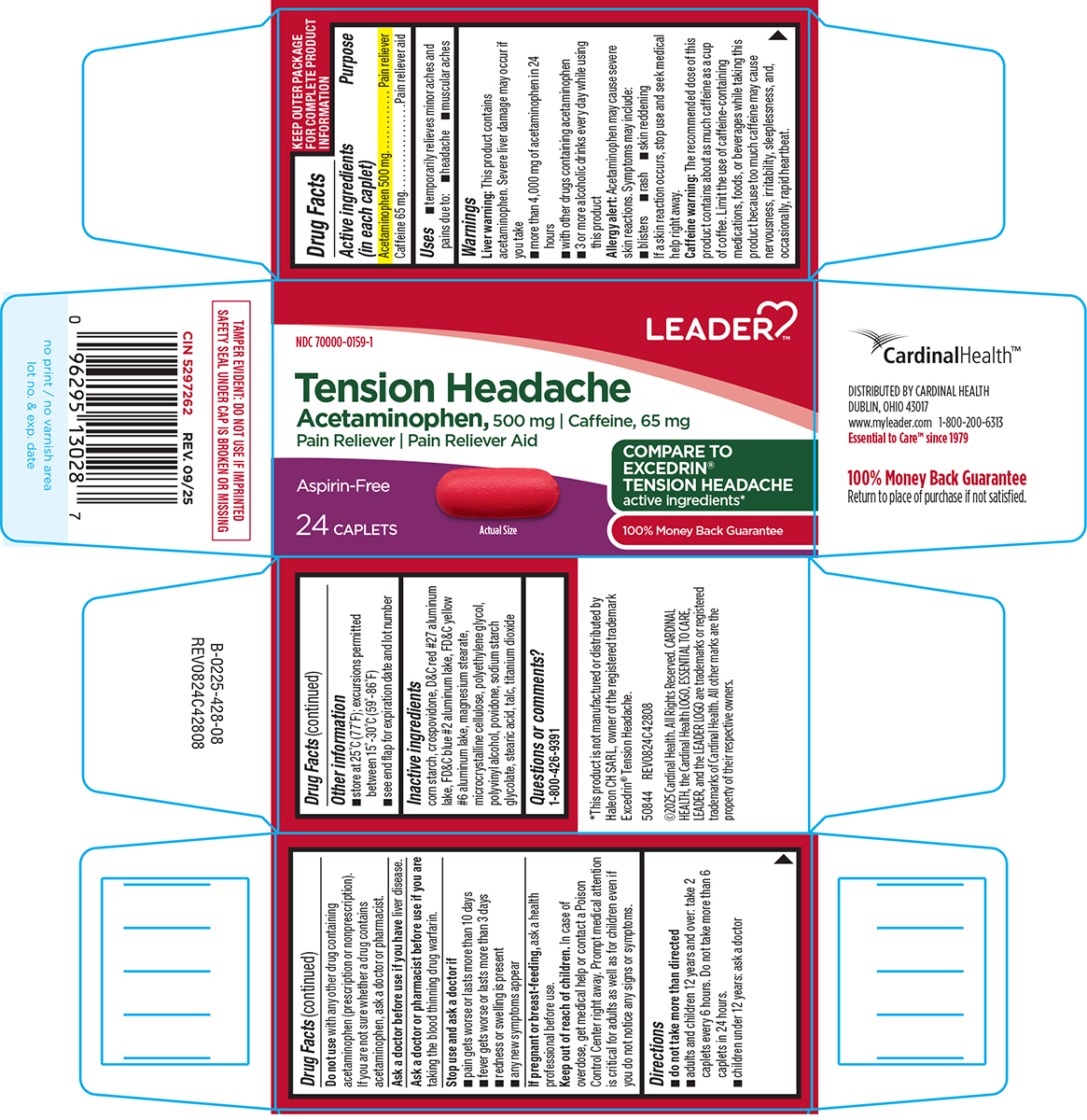 DRUG LABEL: Tension Headache
NDC: 70000-0159 | Form: TABLET, FILM COATED
Manufacturer: Cardinal Health 110, LLC. DBA Leader
Category: otc | Type: HUMAN OTC DRUG LABEL
Date: 20260112

ACTIVE INGREDIENTS: ACETAMINOPHEN 500 mg/1 1; CAFFEINE 65 mg/1 1
INACTIVE INGREDIENTS: STARCH, CORN; CROSPOVIDONE; D&C RED NO. 27 ALUMINUM LAKE; FD&C BLUE NO. 2 ALUMINUM LAKE; FD&C YELLOW NO. 6 ALUMINUM LAKE; MAGNESIUM STEARATE; MICROCRYSTALLINE CELLULOSE; POLYETHYLENE GLYCOL, UNSPECIFIED; POLYVINYL ALCOHOL, UNSPECIFIED; POVIDONE, UNSPECIFIED; SODIUM STARCH GLYCOLATE TYPE A POTATO; STEARIC ACID; TALC; TITANIUM DIOXIDE

Leader 44-428

Active ingredients (in each caplet)

Acetaminophen 500 mg
Caffeine 65 mg

Purpose

Pain reliever
Pain reliever aid

Uses

- temporarily relieves minor aches and pains due to:
  - headache
  - muscular aches

Warnings

Liver warning: This product contains acetaminophen. Severe liver damage may occur if you take

- more than 4,000 mg of acetaminophen in 24 hours
- with other drugs containing acetaminophen
- 3 or more alcoholic drinks every day while using this product

Allergy alert: Acetaminophen may cause severe skin reactions. Symptoms may include:

- blisters
- rash
- skin reddening

If a skin reaction occurs, stop use and seek medical help right away.

Caffeine warning: The recommended dose of this product contains about as much caffeine as a cup of coffee. Limit the use of caffeine-containing medications, foods, or beverages while taking this product because too much caffeine may cause nervousness, irritability, sleeplessness, and, occasionally, rapid heartbeat.

Do not use

with any other drug containing acetaminophen (prescription or nonprescription). If you are not sure whether a drug contains acetaminophen, ask a doctor or pharmacist.

Ask a doctor before use if you have

liver disease.

Ask a doctor or pharmacist before use if you are

taking the blood thinning drug warfarin.

Stop use and ask a doctor if

- any new symptoms appear
- redness or swelling is present
- pain gets worse or lasts for more than 10 days
- fever gets worse or lasts for more than 3 days

If pregnant or breast-feeding,

ask a health professional before use.

Keep out of reach of children.

In case of overdose, get medical help or contact a Poison Control Center right away. Prompt medical attention is critical for adults as well as for children even if you do not notice any signs or symptoms.

Directions

- do not take more than directed
- adults and children 12 years and over: take 2 caplets every 6 hours. Do not take more than 6 caplets in 24 hours.
- children under 12 years: ask a doctor

Other information

- store at 25ºC (77ºF); excursions permitted between 15º-30ºC (59º-86ºF)
- see end flap for expiration date and lot number

Inactive ingredients

corn starch, crospovidone, D&C red #27 aluminum lake, FD&C blue #2 aluminum lake, FD&C yellow #6 aluminum lake, magnesium stearate, microcrystalline cellulose, polyethylene glycol, polyvinyl alcohol, povidone, sodium starch glycolate, stearic acid, talc, titanium dioxide

Questions or comments?

1-800-426-9391

Principal Display Panel

LEADER™

NDC 70000-0159-1

Tension Headache
Acetaminophen, 500 mg
Caffeine, 65 mg
Pain reliever Pain Reliever Aid

Aspirin-Free

COMPARE TO
EXCEDRIN®
TENSION
HEADACHE
active ingredients*

100% Money
Back Guarantee

24 CAPLETS

Actual Size

TAMPER EVIDENT: DO NOT USE IF IMPRINTED
SAFETY SEAL UNDER CAP IS BROKEN OR MISSING

*This product is not manufactured or distributed by
Haleon CH SARL, owner of the registered trademark
Excedrin® Tension Headache.

50844 REV0824C42808

©2025 Cardinal Health. All Rights Reserved. CARDINAL
HEALTH, the Cardinal Health LOGO, ESSENTIAL TO CARE,
LEADER, and the LEADER LOGO are trademarks or registered
trademarks of Cardinal Health. All other marks are the
property of their respective owners.

CardinalHealth™
DISTRIBUTED BY CARDINAL HEALTH
DUBLIN, OHIO 43017
www.myleader.com 1-800-200-6313
Essential to Care™ since 1979

100% Money Back Guarantee
Return to place of purchase if not satisfied.

Leader 44-428